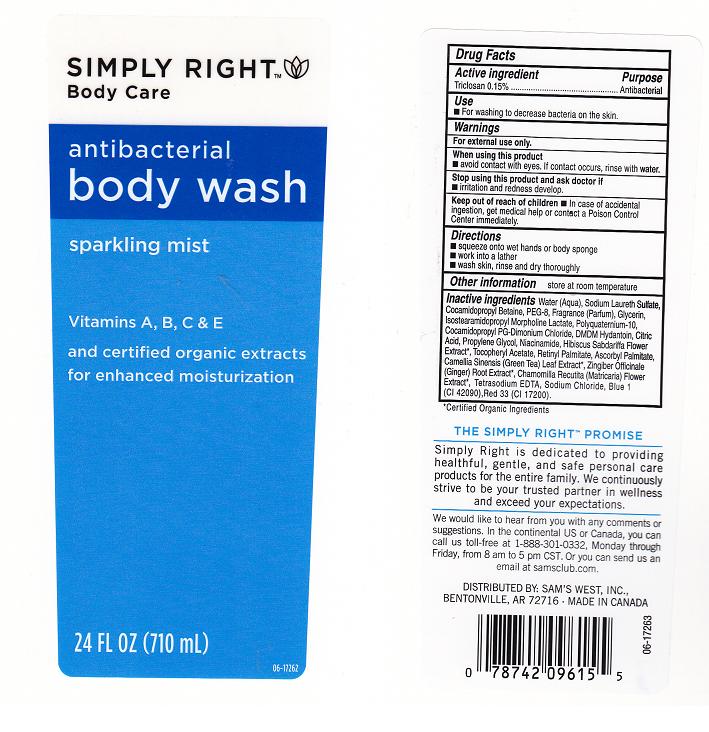 DRUG LABEL: ANTIBACTERIAL
NDC: 68196-804 | Form: SOLUTION
Manufacturer: SAM'S WEST INC
Category: otc | Type: HUMAN OTC DRUG LABEL
Date: 20110617

ACTIVE INGREDIENTS: TRICLOSAN 0.15 mL/100 mL
INACTIVE INGREDIENTS: WATER; SODIUM LAURETH SULFATE; COCAMIDOPROPYL BETAINE; PEG-8 DIOLEATE; GLYCERIN; INDELOXAZINE HYDROCHLORIDE; POLYQUATERNIUM-10 (400 CPS AT 2%); COCAMIDOPROPYL PG-DIMONIUM CHLORIDE PHOSPHATE; DMDM HYDANTOIN; CITRIC ACID MONOHYDRATE; PROPYLENE GLYCOL; NIACINAMIDE; HIBISCUS SABDARIFFA FLOWER; .ALPHA.-TOCOPHEROL ACETATE, DL-; VITAMIN A PALMITATE; ASCORBYL PALMITATE; GREEN TEA LEAF; EDETATE SODIUM; GINGER; CHAMAEMELUM NOBILE FLOWER; SODIUM CHLORIDE; FD&C BLUE NO. 1; D&C RED NO. 33

DRUG FACTS

ACTIVE INGREDIENT

TRICLOSAN 0.15%

PURPOSE

ANTIBACTERIAL

USE

FOR WASHING TO DECREASE BACTERIA ON THE SKIN

WARNINGS

FOR EXTERNAL USE ONLY

WHEN USING THIS PRODUCT

AVOID CONTACT WITH EYES. IF CONTACT OCCURS, RINSE WITH WATER.

STOP USING THIS PRODUCT AND ASK DOCTOR IF

IRRITATION AND REDNESS DEVELOP.

KEEP OUT OF REACH OF CHILDREN

IN CASE OF ACCIDENTAL INGESTION, GET MEDICAL HELP OR CONTACT POISON CONTROL IMMEDIATELY.

DIRECTIONS

SQUEEZE ONTO WET HANDS OR BODY SPONGE, WORK INTO LATHER, WASH SKIN,RINSE AND DRY THOROUGHLY.

OTHER INFORMATION

STORE AT ROOM TEMPERATURE

INACTIVE INGREDIENTS

WATER, SODIUM LAURETH SULFATE, COCAMIDOPROPYL BETAINE, PEG-8, FRAGRANCE, GLYCERIN, ISOSTEARAMIDOPROPYL MORPHOLINE LACTATE, POLYQUATERNIUM-10, COCAMIDOPROPYL PG-DIMONIUM CHLORIDE, DMDM HYDANTOIN, CITRIC ACID, PROPYLENE GLYCOL, NIACINAMIDE, HIBISCUS, SADARIFFA FLOWER EXTRACT, TOCOPHERYL ACETATE, RETINYL PALMITATE, ASCORBYL PALMITATE, CAMELLIA SINENSIS (GREEN TEA) LEAF EXTRACT, ZINGIBER OFFICINALE (GINGER) ROOT EXTRACT, CHAMOMILLA RECUTITA (MATRICARIA) FLOWER EXTRACT, TETRASODIUM EDTA, SODIUM CHLORIDE, BLUE1, RED 33